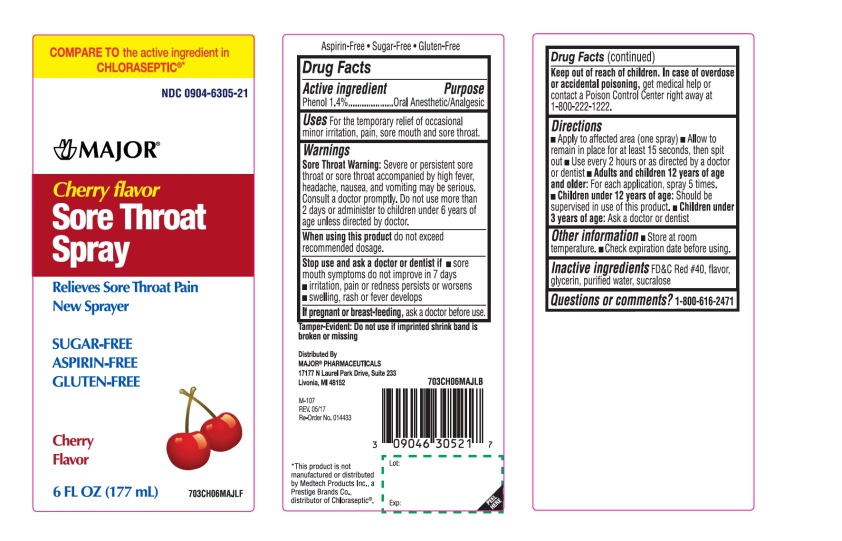 DRUG LABEL: Sore Throat Cherry
NDC: 0904-6305 | Form: LIQUID
Manufacturer: Major Pharmaceuticals
Category: otc | Type: HUMAN OTC DRUG LABEL
Date: 20250919

ACTIVE INGREDIENTS: PHENOL 1.5 g/100 mL
INACTIVE INGREDIENTS: FD&C RED NO. 40; GLYCERIN; WATER; SUCRALOSE

Drug Facts

Active Ingredient

Phenol 1.4%

Purpose

Oral Anesthetic/Analgesic

Uses

For the temporary relief of occasional minor irritation, pain, sore mouth and sore throat.

Warnings

Sore Throat Warning:Severe or persistent sore throat or sore throat accompanied by high fever, headache, nausea, and vomiting may be serious. Consult doctor promptly. Do not use more than 2 days or administer to children under 6 years of age unless directed by doctor.

When using this product

do not exceed recommended dosage.

Stop use and ask a doctor or dentist if

- sore mouth symptoms do not improve in 7 days
- irritation, pain or redness persists or worsens
- swelling, rash or fever develops

If pregnant or breast-feeding

ask a doctor before use.

Drug Facts (continued)

Keep out of the reach of children. In case of overdose or accidental poisoning, get medical help or contact a Poison Control Center right away at 1-800-222-1222.

Directions

- Apply to the affected area (one spray).
- Allow to remain in place for at least 15 seconds then spit out. Use every 2 hours or as directed by a doctor or dentist.
- Adults and children 6 years of age and older:For each application, spray 5 times.
- Children under 12 years of ageshould be supervised in the use of this product.
- Children under 3 years of age: Ask a doctor or dentist.

Other Information

- Store at room temperature
- Check expiration date before using.

Inactive Ingredients

FD&C Red # 40, flavor, glycerin, purified water, sucralose

Questions or comments?

1-800-616-2471

Principal Display Pane

COMPARE TO the active ingredient in CHLORASEPTIC®*

NDC 0904-6305-21

MAJOR®

Cherry flavor

Sore Throat Spray

Relieves Sore Throat Pain

New Sprayer

SUGAR- FREE

ASPIRIN-FREE

GLUTEN-FREE

Cherry Flavor

6 FL OZ (177 mL)

Tamper-Evident: Do not use i9f imprinted shrink band is broken or missing

Distributed By

MAJOR®PHARMACEUTICALS

17177 N Laurel Park Drive, Suite 233

Livonia, MI 48152

This product is not manufactured or distributed by Medtech Products Inc., a Prestige Brands Co., distributor of Chloraseptic®.